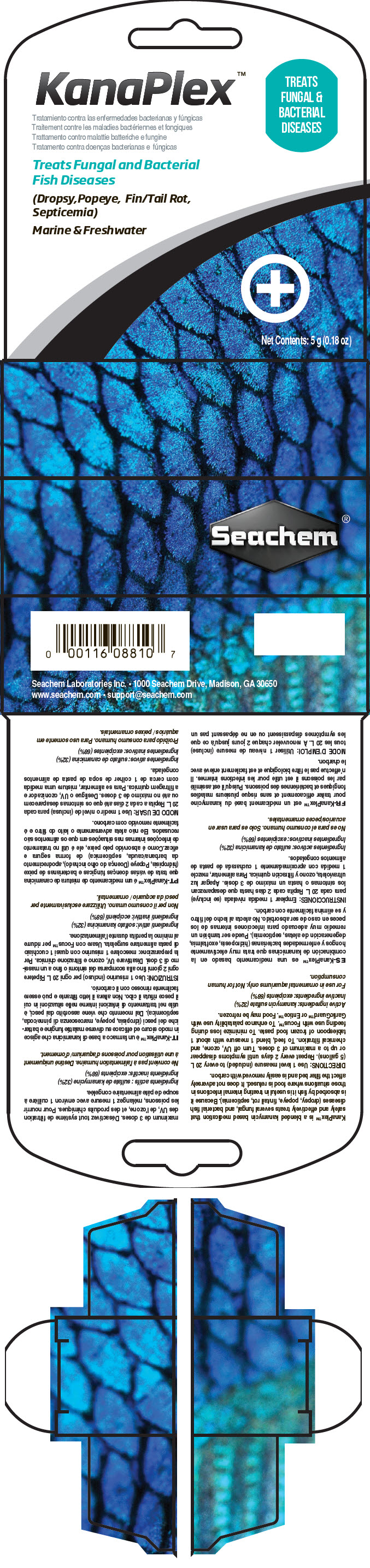 DRUG LABEL: Kanaplex
NDC: 55999-089 | Form: POWDER
Manufacturer: Seachem Laboratories Inc.
Category: animal | Type: OTC ANIMAL DRUG LABEL
Date: 20180713

ACTIVE INGREDIENTS: KANAMYCIN A SULFATE 317 mg/1 g

Kanaplex™

VETERINARY INDICATIONS

KanaPlex™ is a blended kanamycin based medication that safely and effectively treats several fungal, and bacterial fish diseases (dropsy, popeye, fin/tail rot, septicemia). Because it is absorbed by fish it is useful in treating internal infections in those situations where food is refused. It does not adversely affect the filter bed and is easily removed with carbon.

DOSAGE AND ADMINISTRATION

DIRECTIONS: Use 1 level measure (included) to every 20 L (5 gallons). Repeat every 2 days until symptoms disappear or up to a maximum of 3 doses. Turn off UV, ozone, and chemical filtration. To feed, blend 1 measure with about 1 tablespoon of frozen food paste. To minimize loss during feeding use with Focus™. To enhance palatability use with GarlicGuard™ or Entice™. Food may be refrozen.

Active ingredients: kanamycin sulfate (32%)

Inactive ingredients: excipients (68%)

SAFE HANDLING WARNING

For use in ornamental aquariums only. Not for human consumption.

Seachem Laboratories Inc. • 1000 Seachem Drive, Madison, GA 30650

www.seachem.com • support@seachem.com

PRINCIPAL DISPLAY PANEL - 5 g Vial Carton

KanaPlex™

TREATS
FUNGAL &
BACTERIAL
DISEASES

Treats Fungal and Bacterial
Fish Diseases

(Dropsy,Popeye, Fin/Tail Rot,
Septicemia)

Marine & Freshwater

Net Contents: 5 g (0.18 oz)

Seachem®